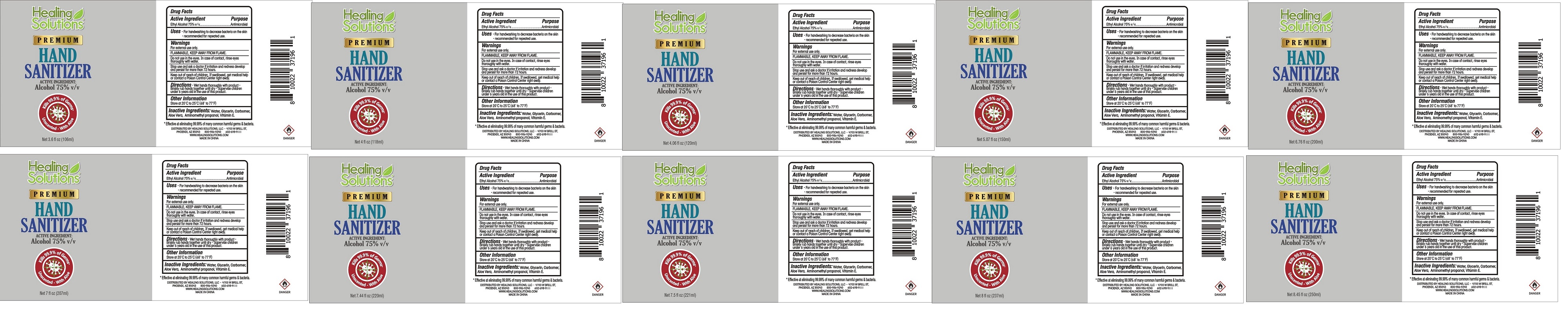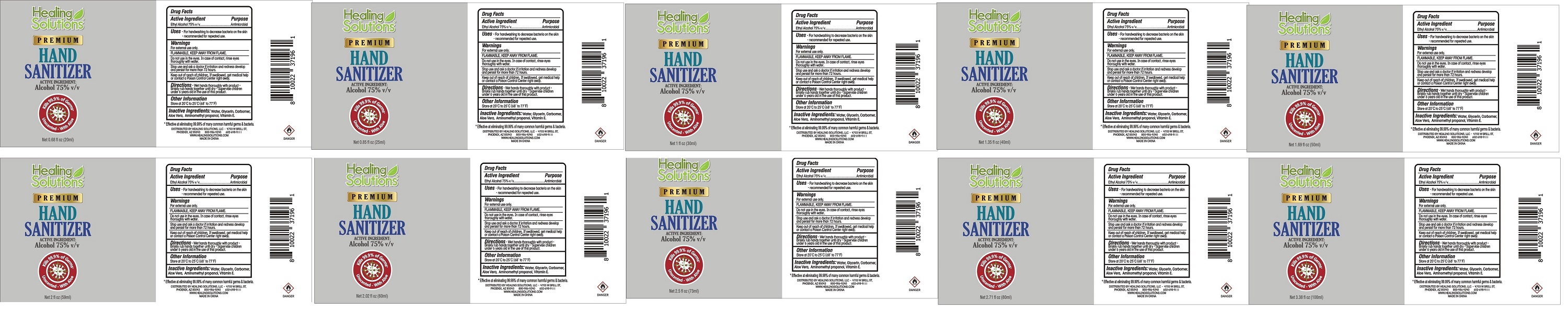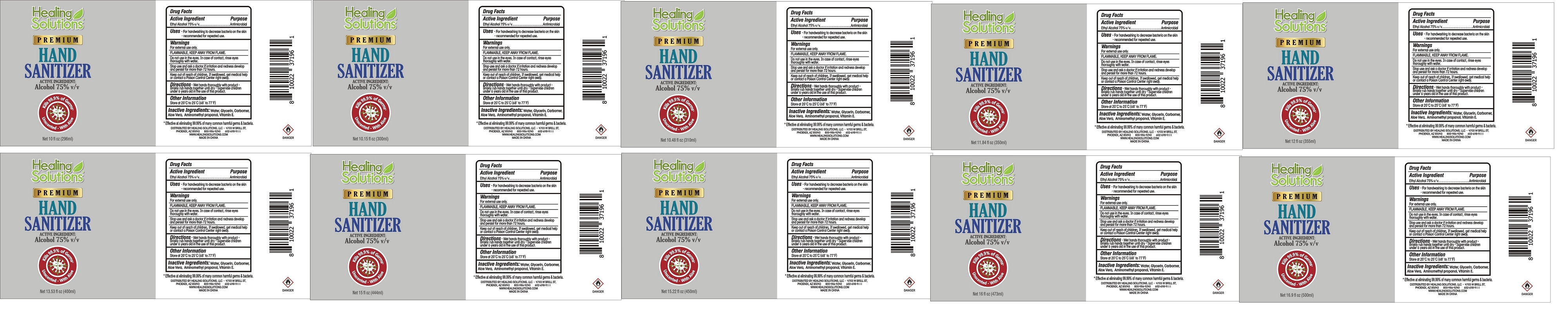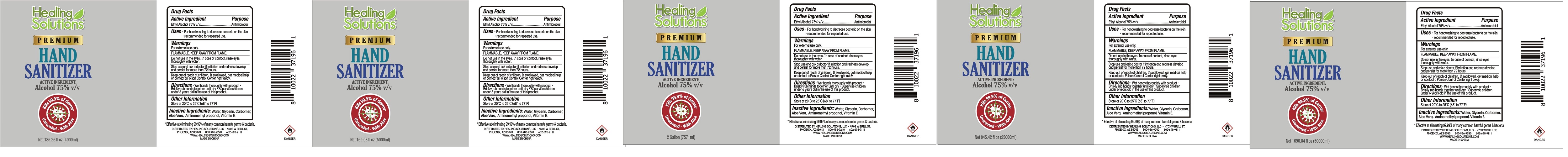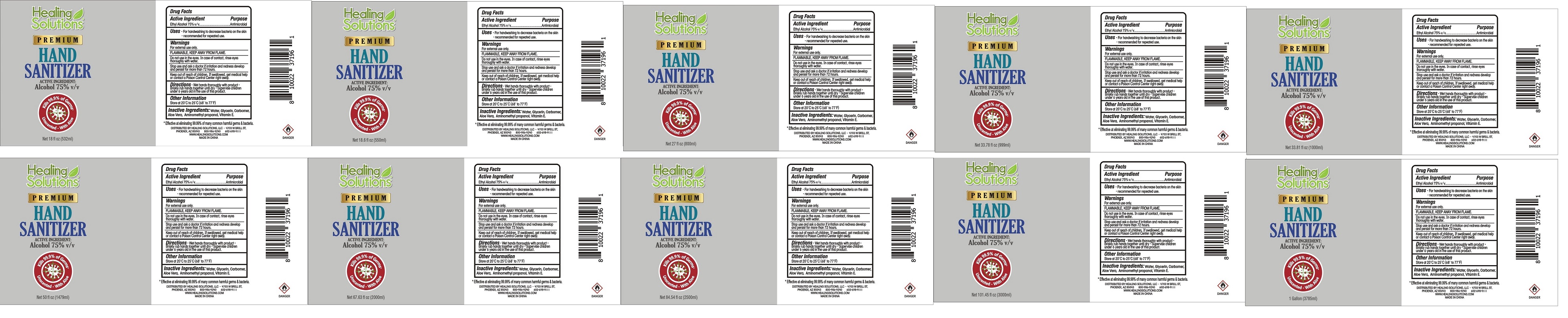 DRUG LABEL: Hand Sanitizer
NDC: 52807-101 | Form: LIQUID
Manufacturer: Guangdong Longtai Industry Co.,LTD
Category: otc | Type: HUMAN OTC DRUG LABEL
Date: 20200727

ACTIVE INGREDIENTS: ALCOHOL 75 mL/100 mL
INACTIVE INGREDIENTS: AMINOMETHYLPROPANOL; ALOE VERA LEAF; .ALPHA.-TOCOPHEROL ACETATE; GLYCERIN; CARBOMER COPOLYMER TYPE A (ALLYL PENTAERYTHRITOL CROSSLINKED); WATER

Active Ingredient

Ethyl Alcohol 75%V/V

Purpose

Purpose: Antimicrobial

Uses

For hand washing to decrease bacteria on the skinre commended for repeated use

Warnings

KEEP AWAY FROM FLAMDo not use in the eyes. In case of contact, rinse eyeswith wafer

- Do not use in the eyes. In case of contact, rinse eye soughly with wafer

WHEN USING

/

Stop use and ask a doctor f irriration and renews develop and persist for more than 72 hours

Keep out of reach of children. If swallowed, get medical help or contact a Poison Control Center right away.

Directions

Wet hands thoroughly with product. briskly rub hans together until dry Supervise children under 6 years old in the use of this product.

Other information

- Store at 20 to 25C(68 to 77 F)

Inactive ingredients

water, Glycerin, CaromAloe vera, Aminomethyl propanol Vitamin E